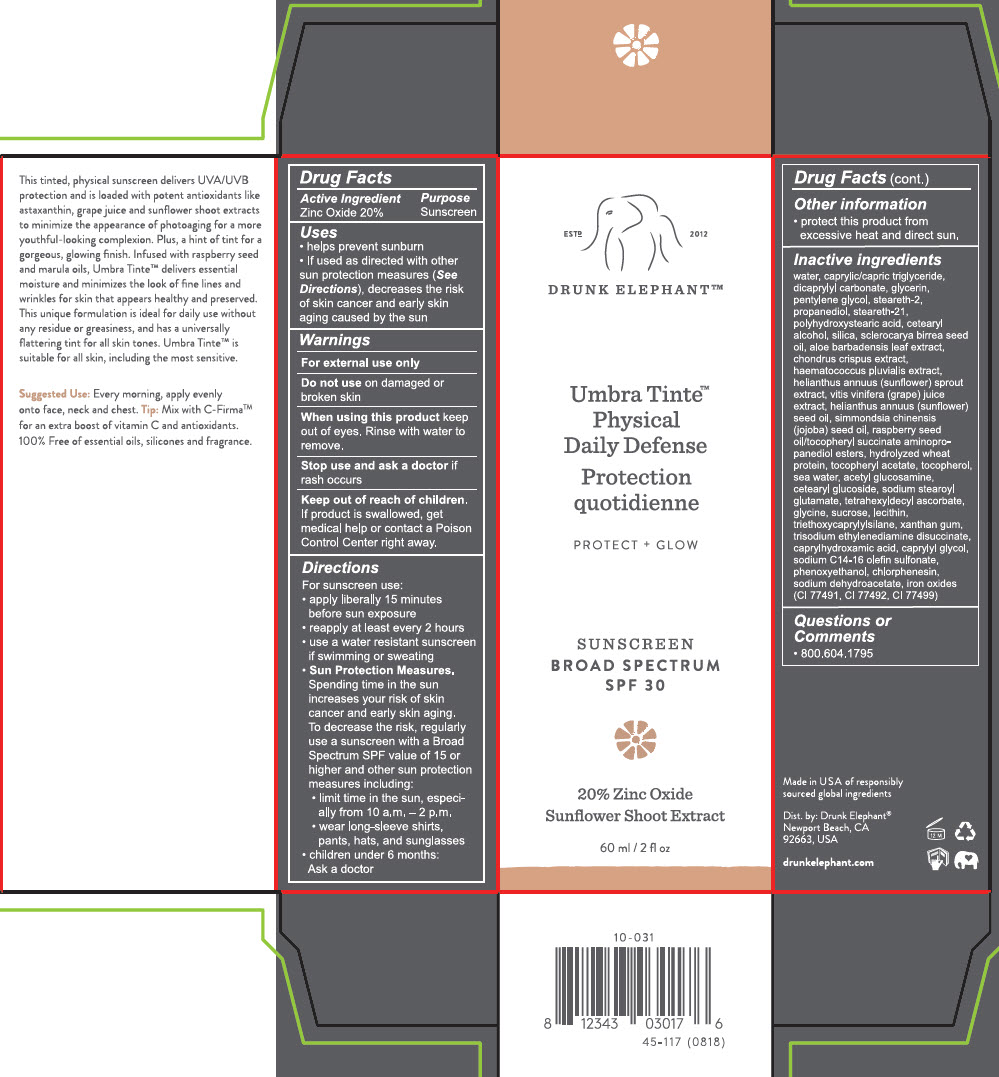 DRUG LABEL: Drunk Elephant
NDC: 69455-463 | Form: LOTION
Manufacturer: Drunk Elephant, LLC
Category: otc | Type: HUMAN OTC DRUG LABEL
Date: 20220808

ACTIVE INGREDIENTS: ZINC OXIDE 20 mg/100 mL
INACTIVE INGREDIENTS: WATER; MEDIUM-CHAIN TRIGLYCERIDES; DICAPRYLYL CARBONATE; GLYCERIN; PENTYLENE GLYCOL; STEARETH-2; PROPANEDIOL; STEARETH-21; POLYHYDROXYSTEARIC ACID (2300 MW); CETOSTEARYL ALCOHOL; SILICON DIOXIDE; SCLEROCARYA BIRREA SEED OIL; ALOE VERA LEAF; CHONDRUS CRISPUS; HAEMATOCOCCUS PLUVIALIS; HELIANTHUS ANNUUS SPROUT; WINE GRAPE JUICE; SUNFLOWER OIL; JOJOBA OIL; RASPBERRY SEED OIL; HYDROLYZED WHEAT PROTEIN (ENZYMATIC; 3000 MW); .ALPHA.-TOCOPHEROL SUCCINATE, D-; AMINOPROPANEDIOL; .ALPHA.-TOCOPHEROL ACETATE; TOCOPHEROL; SODIUM CHLORIDE; N-ACETYLGLUCOSAMINE; CETEARYL GLUCOSIDE; SODIUM STEAROYL GLUTAMATE; TETRAHEXYLDECYL ASCORBATE; GLYCINE; SUCROSE; SODIUM C14-16 OLEFIN SULFONATE; LECITHIN, SUNFLOWER; TRIETHOXYCAPRYLYLSILANE; XANTHAN GUM; TRISODIUM ETHYLENEDIAMINE DISUCCINATE; CAPRYLHYDROXAMIC ACID; CAPRYLYL GLYCOL; PHENOXYETHANOL; CHLORPHENESIN; SODIUM DEHYDROACETATE; FERRIC OXIDE RED; FERRIC OXIDE YELLOW; FERROSOFERRIC OXIDE

Drunk Elephant™
Umbre Tinte™ Physical Daily Defense Protection SPF-30

Drug Facts

Active Ingredient

Zinc Oxide 20%

Purpose

Sunscreen

Uses

- helps prevent sunburn
- If used as directed with other sun protection measures (See Directions), decreases the risk of skin cancer and early skin aging caused by the sun

Warnings

For external use only

Do not use on damaged or broken skin

When using this product keep out of eyes. Rinse with water to remove.

Stop use and ask a doctor if rash occurs

Keep out of reach of children. If product is swallowed, get medical help or contact a Poison Control Center right away.

Directions

For sunscreen use:

- apply liberally 15 minutes before sun exposure
- reapply at least every 2 hours
- use a water resistant sunscreen if swimming or sweating
- Sun Protection Measures. Spending time in the sun increases your risk of skin cancer and early skin aging. To decrease the risk, regularly use a sunscreen with a Broad Spectrum SPF value of 15 or higher and other sun protection measures including:
  - limit time in the sun, especially from 10 a.m. – 2 p.m.
  - wear long-sleeve shirts, pants, hats, and sunglasses
- children under 6 months:
  Ask a doctor

Other information

- protect this product from excessive heat and direct sun.

Inactive ingredients

water, caprylic/capric triglyceride, dicaprylyl carbonate, glycerin, pentylene glycol, steareth-2, propanediol, steareth-21, polyhydroxystearic acid, cetearyl alcohol, silica, sclerocarya birrea seed oil, aloe barbadensis leaf extract, chondrus crispus extract, haematococcus pluvialis extract, helianthus annuus (sunflower) sprout extract, vitis vinifera (grape) juice extract, helianthus annuus (sunflower) seed oil, simmondsia chinensis (jojoba) seed oil, raspberry seed oil/tocopheryl succinate aminopropanediol esters, hydrolyzed wheat protein, tocopheryl acetate, tocopherol, sea water, acetyl glucosamine, cetearyl glucoside, sodium stearoyl glutamate, tetrahexyldecyl ascorbate, glycine, sucrose, lecithin, triethoxycaprylylsilane, xanthan gum, trisodium ethylenediamine disuccinate, caprylhydroxamic acid, caprylyl glycol, sodium C14-16 olefin sulfonate, phenoxyethanol, chlorphenesin, sodium dehydroacetate, iron oxides (CI 77491, CI 77492, CI 77499)

Questions or Comments

- 800.604.1795

Dist. by:
Drunk Elephant®
Newport Beach, CA
92663, USA

PRINCIPAL DISPLAY PANEL - 60 ml Tube Box

ESTD
2012
DRUNK ELEPHANT™

Umbra Tinte™
Physical
Daily Defense

PROTECT + GLOW

SUNSCREEN
BROAD SPECTRUM
SPF 30

20% Zinc Oxide
Sunflower Shoot Extract

60 ml / 2 fl oz